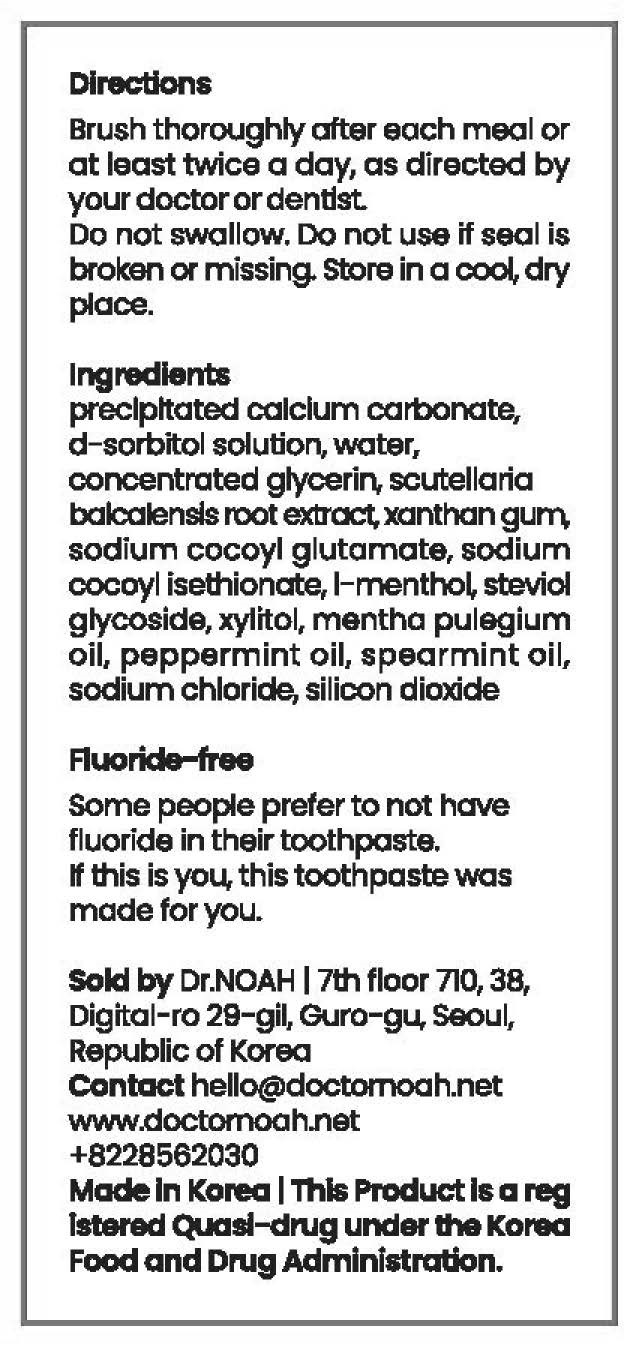 DRUG LABEL: Dr.NOAH MARUTOOTHPASTE
NDC: 82359-0002 | Form: PASTE
Manufacturer: DR.Noah
Category: otc | Type: HUMAN OTC DRUG LABEL
Date: 20211029

ACTIVE INGREDIENTS: CALCIUM CARBONATE 0.22 g/100 g
INACTIVE INGREDIENTS: GLYCERIN; SORBITOL

ACTIVE INGREDIENT

precipitated calcium carbonate

INACTIVE INGREDIENT

d-sorbitol solution, water, concentrated glycerin, scutellaria bak, alensls root extract, xanthan gurn, sodium cocoyl glutamate, sodium
cocoyl isethionate, 1-mentho~ steviol, glycoside, xylitol, mentha pulagium, oil, peppermint oil, spearmint oil, sodium chloride, silicon dioxide

PURPOSE

■ Keeps teeth white and strong

■ Keep the oral cavity clean

■ Prevents tooth decay and bad breath caused by fluoride

■ Removing plaque, preventing gingivitis and periodontitis

■ Periodontal Disease Prevention

■ Gum Disease Prevention

KEEP OUT OF REACH OF CHILDREN

WARNING

For oral use only
When using this product

■ This toothpaste has a 1,000 ppm fluoride content

■ Do not use other than brushing teeth and be careful not to swallow

Keep out of reach of children

■ if swallowed, seek medical help or contact the poison control center immediately

USES

for oral use only

INDICATION & USAGE SECTION

Brush thoroughly ofter each meal or at least twice a day, as directed by yourdoctorordendst
Do not swallow.

Do not use if seal is broken or missing.

store in a cool, dry place.